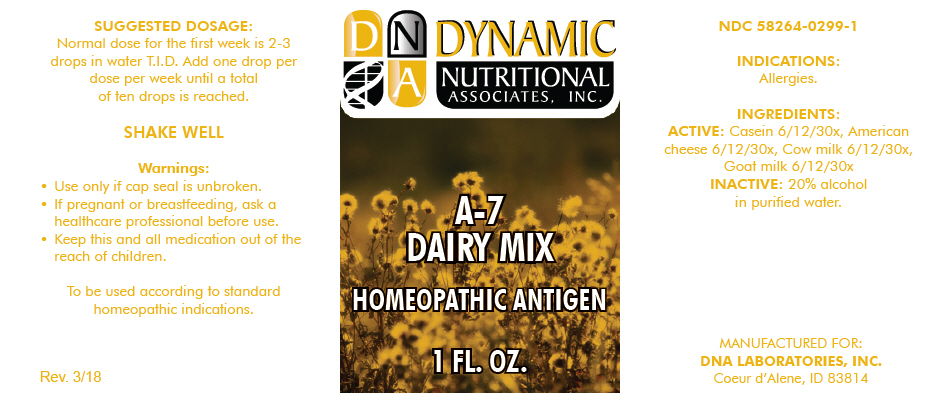 DRUG LABEL: A-7
NDC: 58264-0299 | Form: SOLUTION
Manufacturer: DNA Labs, Inc.
Category: homeopathic | Type: HUMAN OTC DRUG LABEL
Date: 20250109

ACTIVE INGREDIENTS: CASEIN 30 [hp_X]/1 mL; CASEIN, LACTOCOCCUS LACTIS CULTURED, AGED 30 [hp_X]/1 mL; COW MILK 30 [hp_X]/1 mL; GOAT MILK 30 [hp_X]/1 mL
INACTIVE INGREDIENTS: ALCOHOL; WATER

A-7

NDC 58264-0299-1

INDICATIONS

PURPOSE

Allergies.

INGREDIENTS

ACTIVE

Casein 6/12/30x, American cheese 6/12/30x, Cow milk 6/12/30x, Goat milk 6/12/30x

INACTIVE

20% alcohol in purified water.

SUGGESTED DOSAGE

Normal dose for the first week is 2-3 drops in water T.I.D. Add one drop per dose per week until a total of ten drops is reached.

STORAGE AND HANDLING

SHAKE WELL

Warnings

- Use only if cap seal is unbroken.

PREGNANCY OR BREAST FEEDING

- If pregnant or breastfeeding, ask a healthcare professional before use.

KEEP OUT OF REACH OF CHILDREN

- Keep this and all medication out of the reach of children.

To be used according to standard homeopathic indications.

PRINCIPAL DISPLAY PANEL - 1 FL. OZ. Bottle Label

DYNAMIC
NUTRITIONAL
ASSOCIATES, INC.

A-7
DAIRY MIX

HOMEOPATHIC ANTIGEN

1 FL. OZ.